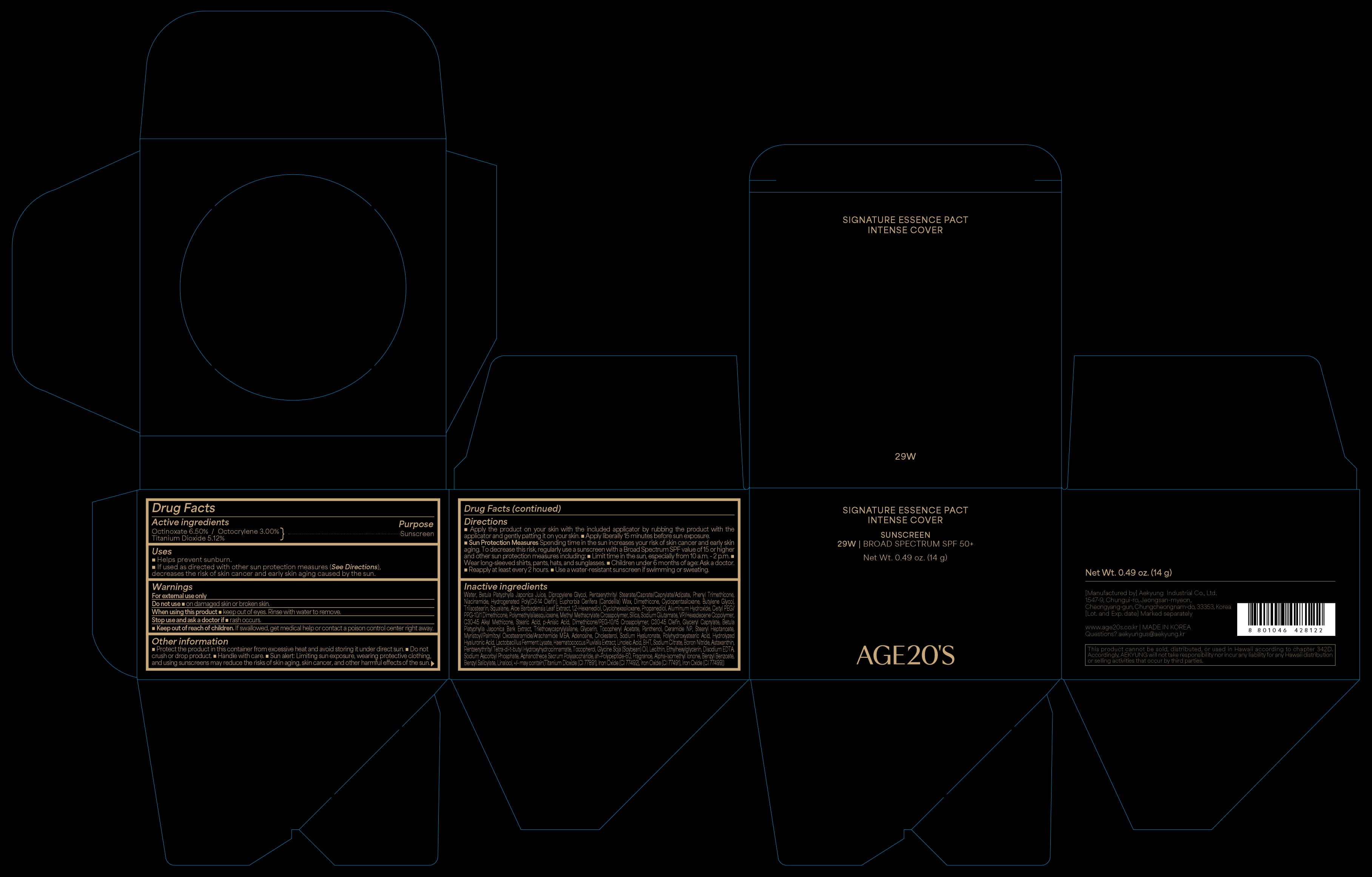 DRUG LABEL: AGE20S SIGNATURE ESSENCE PACT INTENSE COVER 29W
NDC: 67225-5129 | Form: CREAM
Manufacturer: Aekyung Industrial Co., Ltd.
Category: otc | Type: HUMAN OTC DRUG LABEL
Date: 20251209

ACTIVE INGREDIENTS: TITANIUM DIOXIDE 0.7168 g/14 g; OCTINOXATE 0.91 g/14 g; OCTOCRYLENE 0.42 g/14 g
INACTIVE INGREDIENTS: GLYCERYL CAPRYLATE; P-ANISIC ACID; CETYL PEG/PPG-10/1 DIMETHICONE (HLB 2); HYDROGENATED POLY(C6-14 OLEFIN; 2 CST); C30-45 OLEFIN; CHOLESTEROL; HYALURONATE SODIUM; CANDELILLA WAX; ALPHA-TOCOPHEROL ACETATE; ETHYLHEXYLGLYCERIN; ALUMINUM OXIDE; CYCLOMETHICONE 5; PROPANEDIOL; NIACINAMIDE; POLYHYDROXYSTEARIC ACID STEARATE; STEARYL HEPTANOATE; STEARIC ACID; GLYCERIN; ASTAXANTHIN; ALUMINUM HYDROXIDE; FERRIC OXIDE YELLOW; FERROSOFERRIC OXIDE; DIETHYLAMINO HYDROXYBENZOYL HEXYL BENZOATE; HAEMATOCOCCUS PLUVIALIS; 1,2-HEXANEDIOL; LINOLEIC ACID; HYDROGENATED SOYBEAN LECITHIN; DIMETHICONE; POLYMETHYLSILSESQUIOXANE (11 MICRONS); VINYLPYRROLIDONE/HEXADECENE COPOLYMER; SOYBEAN OIL; WATER; SQUALANE; BUTYLENE GLYCOL; FERRIC OXIDE RED; DIPROPYLENE GLYCOL; HYALURONIC ACID; TRIISOSTEARIN; CYCLOMETHICONE 6; CERAMIDE NP; BORON NITRIDE; BETULA PLATYPHYLLA RESIN; MONOSODIUM GLUTAMATE; C30-45 ALKYL METHICONE; PANTHENOL; PHENYL TRIMETHICONE; TRIETHOXYCAPRYLYLSILANE; ALOE VERA LEAF; BETULA PLATYPHYLLA BARK; MYRISTOYL/PALMITOYL OXOSTEARAMIDE/ARACHAMIDE MEA; ADENOSINE

67225-5129-2 AGE20S SIGNATURE ESSENCE PACT INTENSE COVER 29W

ACTIVE INGREDIENT

Octinoxate 6.50 %

Octocrylene 3.00 %

Titanium Dioxide 5.12 %

PURPOSE

Sunscreen

INDICATIONS AND USAGE

Helps prevent sunburn.

WARNINGS

For external use only.

DO NOT USE

damaged skin or broken skin.

WHEN USING

keep out of eyes. Rinse with water to remove.

KEEP OUT OF REACH OF CHILDREN

If swallowed, get medical help or contact a poison control center right away.

DOSAGE AND ADMINISTRATION

■ Apply the product on your skin with the included applicator by rubbing the product with the applicator and gently patting it on your skin.
■ Apply liberally 15 minutes before sun exposure.

Sun Protection Measures. Spending time in the sun increases your risk of skin cancer and early skin aging. To decrease this risk, regularly use a sunscreen with a Broad Spectrum SPF value of 15 or higher and other sun protection measures including:

· Limit time in the sun, especially from 10 a.m. - 2 p.m.

· Wear long-sleeved shirts, pants, hats, and sunglasses.

■ Children under 6 months of age: Ask a doctor.
■ Reapply at least every 2 hours.
■ Use a water-resistant sunscreen if swimming or sweating.

STORAGE AND HANDLING

■ Protect the product in this container from excessive heat and avoid storing it under direct sun.

■ Do not crush or drop product.

■ Handle with care.

■ Sun alert: Limiting sun exposure, wearing protective clothing, and using sunscreens may reduce the risks of skin aging, skin cancer, and other harmful effects of the sun.

INACTIVE INGREDIENT

Betula Platyphylla Japonica Bark Extract, Betula Platyphylla Japonica Juice, Dipropylene Glycol, Diethylamino Hydroxybenzoyl Hexyl Benzoate, Phenyl Trimethicone, Niacinamide, Hydrogenated Poly(C6-14 Olefin), Euphorbia Cerifera (Candelilla) Wax, Dimethicone, Cyclopentasiloxane, Butylene Glycol, Squalane, Aloe Barbadensis Leaf Extract, Triisostearin, 1,2-Hexanediol, Cyclohexasiloxane, Polymethylsilsesquioxane, Propanediol, Cetyl PEG/PPG-10/1 Dimethicone, Sodium Glutamate, VP/Hexadecene Copolymer, Aluminum Hydroxide, C30-45 Alkyl Methicone, p-Anisic Acid, Dimethicone/PEG-10/15 Crosspolymer, Stearic Acid, C30-45 Olefin, Glyceryl Caprylate, Glycerin, Triethoxycaprylylsilane, Alumina, Tocopheryl Acetate, Panthenol, Ceramide NP, Stearyl Heptanoate, Myristoyl/Palmitoyl Oxostearamide/Arachamide MEA, Adenosine, Cholesterol, Water, Sodium Hyaluronate, Polyhydroxystearic Acid, Hydrolyzed Hyaluronic Acid, Lactobacillus Ferment Lysate, Haematococcus Pluvialis Extract, Linoleic Acid, Boron Nitride, Astaxanthin, Aphanothece Sacrum Polysaccharide, Glycine Soja (Soybean) Oil, Lecithin, Ethylhexylglycerin, sh-Polypeptide-60, Fragrance, Alpha-Isomethyl Ionone, Benzyl Benzoate, Benzyl Salicylate, Linalool, +/- may contain (Titanium Dioxide (CI 77891), Iron Oxides (CI 77491), Iron Oxides (CI 77492), Iron Oxides (CI 77499))